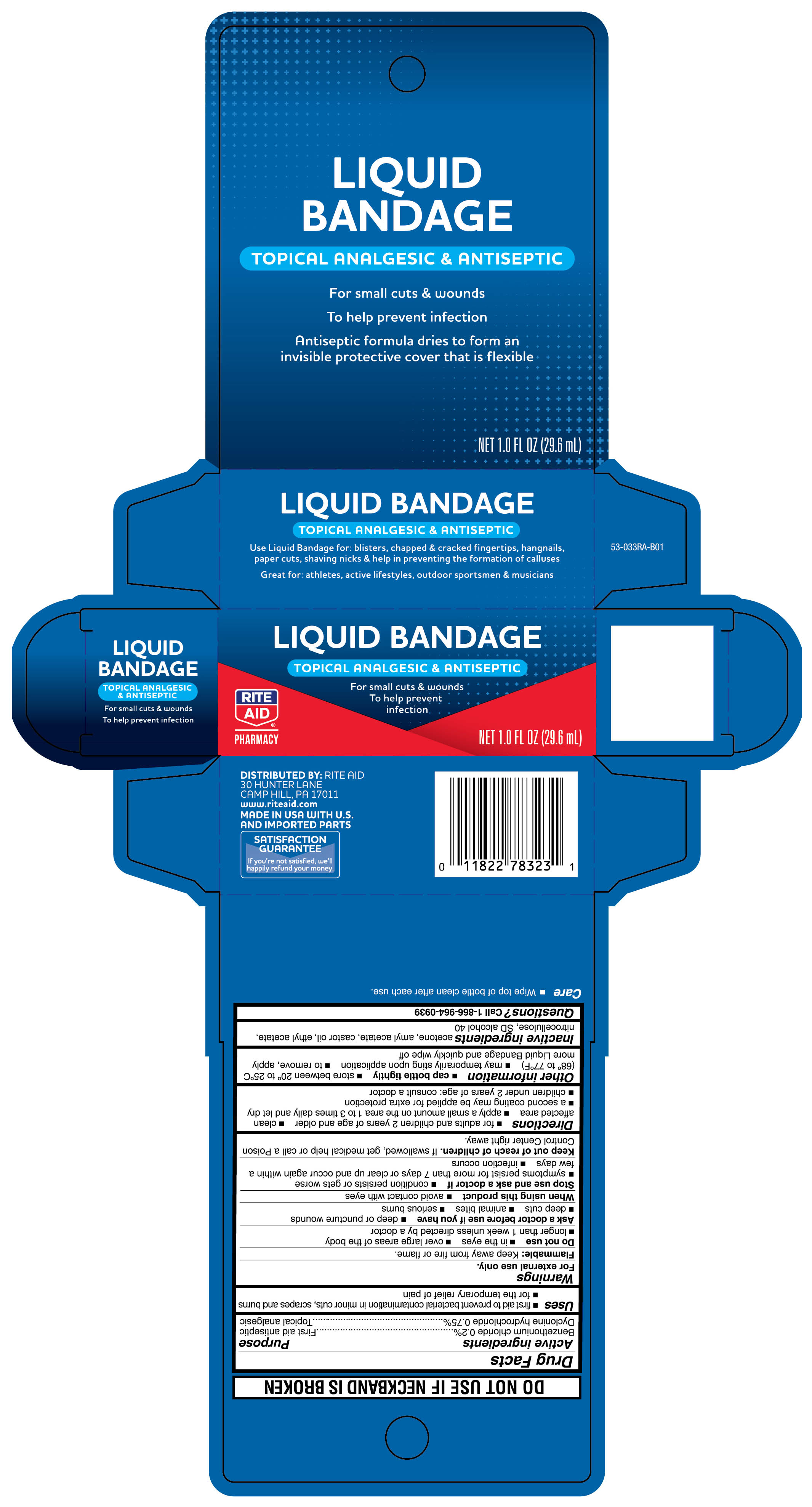 DRUG LABEL: Benzethonium Chloride and Dyclonine Hydrochloride
NDC: 11822-0779 | Form: LIQUID
Manufacturer: Rite Aid Corporation
Category: otc | Type: HUMAN OTC DRUG LABEL
Date: 20250621

ACTIVE INGREDIENTS: BENZETHONIUM CHLORIDE 0.2 mg/30 mL; DYCLONINE HYDROCHLORIDE 0.75 mg/30 mL
INACTIVE INGREDIENTS: PYROXYLIN; ETHYL ACETATE; ACETONE; AMYL ACETATE; CASTOR OIL; ALCOHOL

Liquid Bandage 1 fl oz (30 mL)

Active ingredient

Benzethonium chloride 0.2%

Dyclonine hydrochoride 0.75%

Purpose

First aid antiseptic

Topical analgesic

Uses

- first aid to prevent bacterial contamination in minor cuts, scrapes and burns
- for temporary relief of pain

Warnings

For external use only.

Flammable:

Keep away from fire or flame.

Do not use

- in the eyes
- over large areas of the body
- longer than 1 week unless directed by a doctor

Ask a doctor before use if you have

- deep or puncture wounds
- deep cuts
- animal bites
- serious burns

When using this product

- avoid contact with eyes

Stop use and ask a doctor if

- condition persists or gets worse
- symptoms persists for more than 7 days or clear up and occur again within a few days
- infection occurs

Keep out of reach of children.

If swallowed, get medical help or call a Poison Control Center right away.

Directions

- for adults and children 2 years of age or older
- clean affected area
- apply a smalll amount on the area 1 to 3 times daily and let dry
- a second coating may be applied for extra protection
- children under 2 years of age: consult a doctor

Other information

- cap bottle tightly
- store between 20° to 25°C (68° to 77°F)
- may temporarily sting upon application
- to remove, apply more Liquid Bandage and quickly wipe off

Inactive ingredients

acetone, amyl acetate, castor oil, ethyl acetate, nitrocellulose, SD alcohol 40

Questions?

Call 1-866-964-0939

Principal Display Panel

Rite Aid

LIQUID BANDAGE

TOPICAL ANALGESIC & ANTISEPTIC

For small cuts & wounds

To help prevent infection

Antiseptic formula dries to form an invisible protective cover that is flexible

NET 1.0 FL OZ (29.6 mL)

Use Liquid Bandage for blisters, chapped & cracked fingertips, hangnails, paper cuts, shaving nicks, & help in preventing the formulation of calluses

Great for: athletes, active lifestyles, outdoor sportsmen & musicians